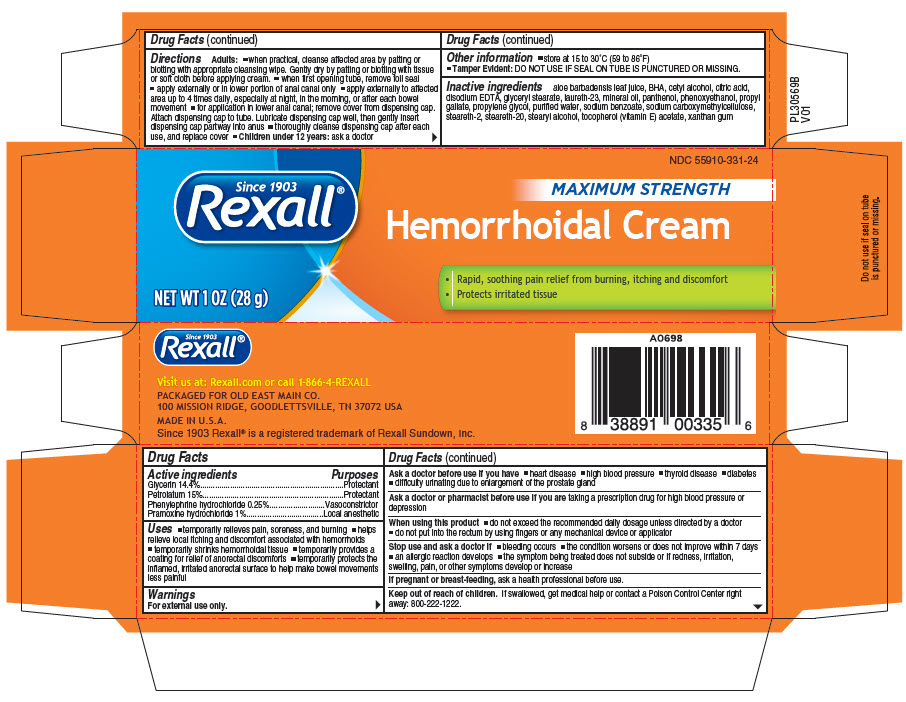 DRUG LABEL: Rexall Hemorrhoidal
NDC: 55910-331 | Form: CREAM
Manufacturer: Dolegencorp,LLC
Category: otc | Type: HUMAN OTC DRUG LABEL
Date: 20241217

ACTIVE INGREDIENTS: Glycerin 0.144 mg/1 g; Phenylephrine Hydrochloride 0.0025 mg/1 g; Pramoxine Hydrochloride 0.1 mg/1 g; Petrolatum 0.15 mg/1 g
INACTIVE INGREDIENTS: Aloe Vera Leaf; Butylated Hydroxyanisole; CARBOXYMETHYLCELLULOSE SODIUM, UNSPECIFIED; Cetostearyl Alcohol; Citric Acid Monohydrate; Edetate Disodium; Glyceryl Monostearate; Laureth-23; Mineral Oil; Panthenol; Propyl Gallate; Propylene Glycol; Sodium Benzoate; Steareth-2; Steareth-20; Stearyl Alcohol; Tocopherol; .Alpha.-Tocopherol; Water; Xanthan Gum

Rexall® Hemorrhoidal Cream
Topical

Drug Facts

ACTIVE INGREDIENT

PURPOSE

Active ingredients | Purposes
Glycerin 14.4% | Protectant
Petrolatum 15% | Protectant
Phenylephrine hydrochloride 0.25% | Vasoconstrictor
Pramoxine hydrochloride 1% | Local anesthetic

Uses

- temporarily relieves pain, soreness, and burning
- helps relieve local itching and discomfort associated with hemorrhoids
- temporarily shrinks hemorrhoidal tissue
- temporarily provides a coating for relief of anorectal discomforts
- temporarily protects the inflamed, irritated anorectal surface to help make bowel movements less painful

Warnings

For external use only.

Ask a doctor before use if you have

- heart disease
- high blood pressure
- thyroid disease
- diabetes
- difficulty urinating due to enlargement of the prostate gland

Ask a doctor or pharmacist before use if you are taking a prescription drug for high blood pressure or depression

When using this product

- do not exceed the recommended daily dosage unless directed by a doctor
- do not put into the rectum by using fingers or any mechanical device or applicator

Stop use and ask a doctor if

- bleeding occurs
- the condition worsens or does not improve within 7 days
- an allergic reaction develops
- the symptom being treated does not subside or if redness, irritation, swelling, pain, or other symptoms develop or increase

PREGNANCY OR BREAST FEEDING

If pregnant or breast-feeding, ask a health professional before use.

Keep out of reach of children. If swallowed, get medical help or contact a Poison Control Center right away: 800-222-1222.

Directions

Adults:

- when practical, cleanse affected area by patting or blotting with appropriate cleansing wipe. Gently dry by patting or blotting with tissue or soft cloth before applying cream.
- when first opening tube, remove foil seal
- apply externally or in lower portion of anal canal only
- apply externally to affected area up to 4 times daily, especially at night, in the morning, or after each bowel movement
- for application in lower anal canal; remove cover from dispensing cap. Attach dispensing cap to tube. Lubricate dispensing cap well, then gently insert dispensing cap partway into anus
- thoroughly cleanse dispensing cap after each use, and replace cover
- Children under 12 years: ask a doctor

Other information

- store at 15 to 30°C (59 to 86°F)
- Tamper Evident: DO NOT USE IF SEAL ON TUBE IS PUNCTURED OR MISSING.

Inactive ingredients

aloe barbadensis leaf juice, BHA, cetyl alcohol, citric acid, disodium EDTA, glyceryl stearate, laureth-23, mineral oil, panthenol, phenoxy ethenol, propyl gallate, propylene glycol, purified water, sodium benzoate, sodium carboxymethylcellulose, steareth-2, steareth-20, stearyl alcohol, tocopherol (vitamin E) acetate, xanthan gum

PRINCIPAL DISPLAY PANEL - 28 g Tube Carton

NDC 55910-331-24

Since 1903
Rexall®

MAXIMUM STRENGTH

Hemorrhoidal Cream

- Rapid, soothing pain relief from burning, itching and discomfort
- Protects irritated tissue

NET WT 1 OZ (28 g)